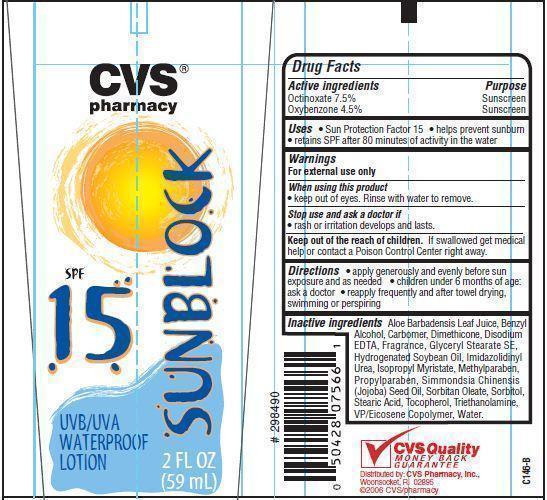 DRUG LABEL: CVS Pharmacy SPF 15
NDC: 59779-025 | Form: LOTION
Manufacturer: CVS Pharmacy
Category: otc | Type: HUMAN OTC DRUG LABEL
Date: 20121219

ACTIVE INGREDIENTS: OCTINOXATE 7.5 g/100 g; OXYBENZONE 4.5 g/100 g
INACTIVE INGREDIENTS: WATER; STEARIC ACID; SORBITOL; SORBITAN MONOOLEATE; GLYCERYL STEARATE SE; HYDROGENATED SOYBEAN OIL; ISOPROPYL MYRISTATE; TROLAMINE; BENZYL ALCOHOL; IMIDUREA; METHYLPARABEN; DIMETHICONE; JOJOBA OIL; PROPYLPARABEN; TOCOPHEROL; EDETATE DISODIUM; ALOE VERA LEAF

Drug Facts

Active ingredients

Octinoxate 7.5%
Oxybenzone 4.5%

Purpose

Sunscreen

Uses

- Sun Protection Factor 15
- helps prevent sunburn
- retains SPF after 80 minutes of activity in water

Warnings

For external use only

When using this product

- keep out of eyes. Rinse with water to remove.

Stop use and ask a doctor if

- rash or irritation develops and lasts.

Keep out of the reach of children.
If swallowed get medical help or contact a Poison Control Center right away.

Directions

- apply generously and evenly before sun exposure and as needed
- children under 6 months of age: ask a doctor
- reapply frequently and after towel drying, swimming or perspiring

Inactive ingredients

Water, Stearic Acid, Sorbitan Oleate, Sorbitol, Glyceryl Stearate SE, Hydrogenated Soybean Oil, Isopropyl Myristate, Triethanolamine, VP/Eicosene Copolymer, Benzyl Alcohol, Dimethicone, Carbomer, Simmondsia Chinensis (Jojoba) Seed Oil, Tocopherol, Disodium EDTA, Aloe Barbadensis Leaf Juice, Imidazolidinyl Urea, Methylparaben, Propylparaben, Fragrance.

Principal Display Panel

CVS
pharmacy
SUNBLOCK
SPF 15
UVA/UVB WATERPROOF LOTION
2 FL OZ (59 mL)